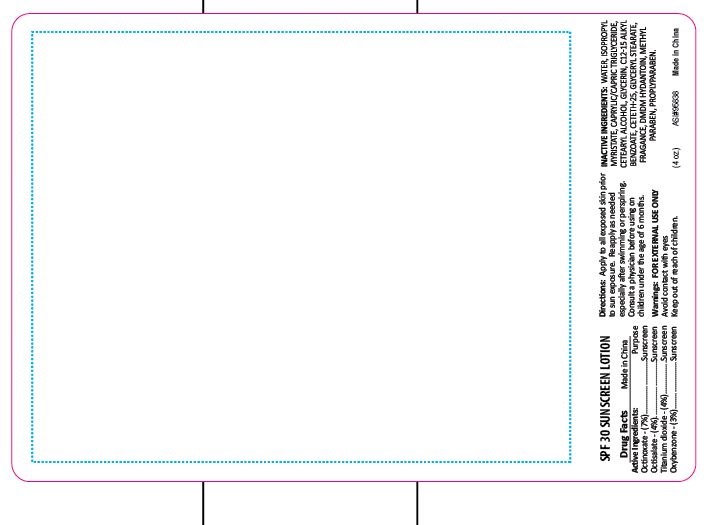 DRUG LABEL: Sun Screen
NDC: 70445-157 | Form: LOTION
Manufacturer: Webb Business Promotions
Category: otc | Type: HUMAN OTC DRUG LABEL
Date: 20220104

ACTIVE INGREDIENTS: TITANIUM DIOXIDE 4 g/100 g; OCTINOXATE 7 g/100 g; OCTISALATE 4 g/100 g; OXYBENZONE 3 g/100 g
INACTIVE INGREDIENTS: DMDM HYDANTOIN; PROPYLPARABEN; GLYCERYL STEARATE SE; CETETH-25; CETOSTEARYL ALCOHOL; CAPRYLIC/CAPRIC/LAURIC TRIGLYCERIDE; GLYCERIN; ALKYL (C12-15) BENZOATE; ISOPROPYL MYRISTATE; WATER; METHYLPARABEN

4oz SPF 30 Sunscreen Lotion

Purpose

Sun Screen

Drug Facts

Octinoxate 7.0%

Octisalate 4.0%

Titanium Dioxide 4.0%

Benzophenone 3.0%

Directions

Apply to all exposed skin prior to sun exposure. Reapply as needed especially after swimming or perspiring. Consult a physician before using on children under the age of 6 months.

Warnings

FOR EXTERNAL USE ONLY

Avoid contact with eyes

Keep out of reach of children

Inactive Ingredients

Water, Isopropyl Myristate, Caprylic/Capric Triglyceride, Cetostearyl Alcohol, Glycerin, Alkyl (C12-15) Benzoate, Ceteth-25, Glyceryl Stearate, Fragrance, DMDM Hydantoin, Methylparaben, Proplyparaben